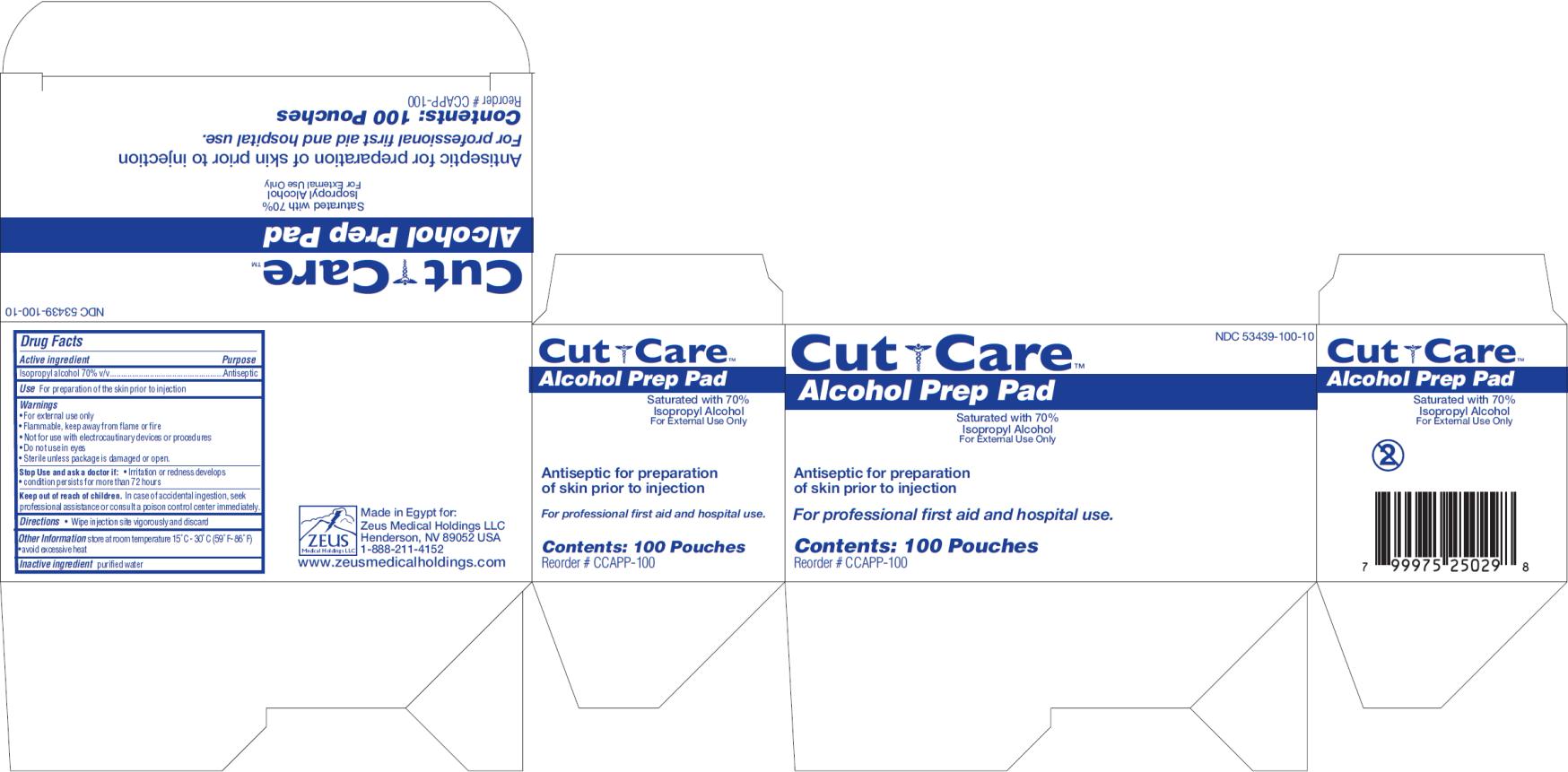 DRUG LABEL: Cut Care Alcohol Prep Pad
NDC: 53439-100 | Form: SWAB
Manufacturer: Zeus Medical Holdings LLC
Category: otc | Type: HUMAN OTC DRUG LABEL
Date: 20130909

ACTIVE INGREDIENTS: ISOPROPYL ALCOHOL 0.7 mL/1 1
INACTIVE INGREDIENTS: WATER

Cut Care Alcohol Prep Pad

Active ingredient

Isopropyl alcohol 70% v/v

Purpose

Antiseptic

Use

For preparation of the skin prior to injection

Warnings

- For external use only
- Flammable, keep away from flame or fire
- Not for use with electrocautinary devices or procedures
- Do not use in eyes
- Sterile unless package is damaged or open.

Stop use and ask a doctor if:

- Irritation or redness develops
- condition persists for more than 72 hours

Keep out of reach of children.

In case of accidental ingestion, seek professional assistance or consult a poison control center immediately.

Directions

- Wipe injection site vigorously and discard

Other information

store at room temperature: 15○ - 30○C (59○F – 86○F)

- avoid excessive heart

Inactive Ingredient

purified water

PRINCIPAL DISPLAY PANEL

NDC 53439-100-10
Cut Care
Alcohol Prep Pad
Saturated with 70% Isopropyl Alcohol
Contents: 100 Pouches